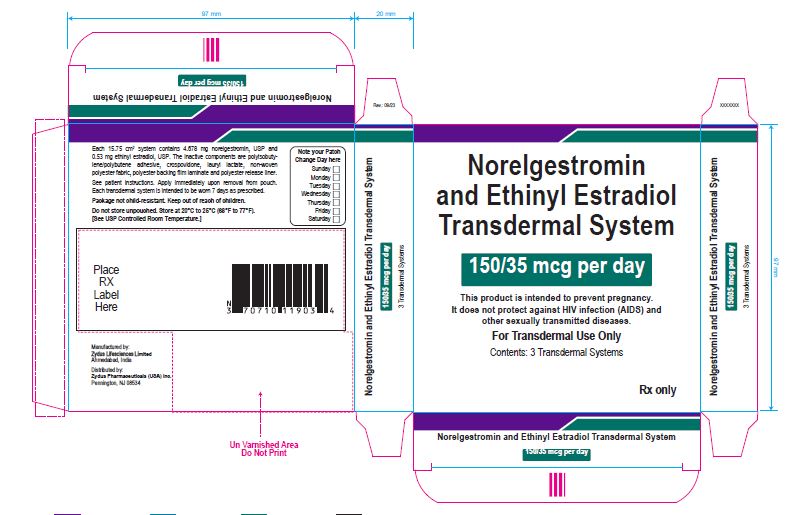 DRUG LABEL: norelgestromin and ethinyl estradiol
NDC: 70771-1777 | Form: PATCH
Manufacturer: Zydus Lifesciences Limited
Category: prescription | Type: HUMAN PRESCRIPTION DRUG LABEL
Date: 20230916

ACTIVE INGREDIENTS: NORELGESTROMIN 150 ug/1 mg; ETHINYL ESTRADIOL 35 ug/1 mg
INACTIVE INGREDIENTS: CROSPOVIDONE; LAURYL LACTATE

NORELGESTROMIN AND ETHINYL ESTRADIOL transdermal system

PACKAGE LABEL.PRINCIPAL DISPLAY PANEL

NDC 70771-1777-3

Norelgestromin and Ethinyl Estradiol Transdermal System 150/35 mcg per day

This product is intended to prevent pregnancy. It does not protect against HIV infection (AIDS) and other sexually transmitted diseases.

For Transdermal Use Only

Contents: 3 Transdermal Systems

Rx only

Each 15.75 cm^2 system contains 4.678 mg norelgestromin, USP and 0.53 mg ethinyl estradiol, USP. The inactive components are polyisobutylene/polybutene adhesive, crospovidone, lauryl lactate, non-woven polyester fabric, polyester backing film laminate and polyester release liner.

See patient instructions. Apply immediately upon removal from pouch. Each transdermal system is intended to be worn 7 days as prescribed.

Package not child-resistant. Keep out of reach of children.

Do not store unpouched. Store at 20° to 25°C (68° to 77°F). [See USP Controlled Room Temperature.]

Manufactured by:

Zydus Lifesciences Ltd.

Ahmedabad, India

Distributed by:

Zydus Pharmaceuticals (USA) Inc.

Pennington, NJ 08534

Rev.: 10/22